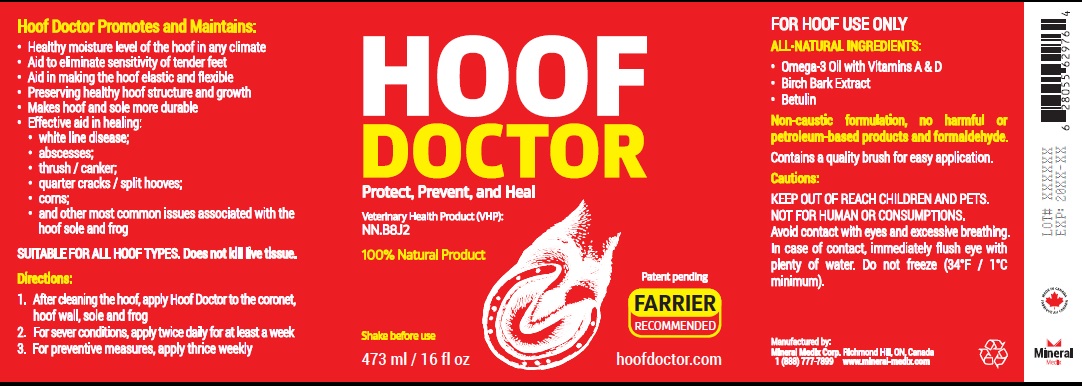 DRUG LABEL: Hoof Doctor
NDC: 86128-002 | Form: OINTMENT
Manufacturer: Mineral Medix Corp.
Category: animal | Type: OTC ANIMAL DRUG LABEL
Date: 20201210

ACTIVE INGREDIENTS: OMEGA-3 FATTY ACIDS 79 g/100 mL; BETULA PUBESCENS BARK 20 g/100 mL; BETULIN 1 g/100 mL

Active Ingredient

Omega-3 Fatty Acid, Betula Pubescens Bark, Betulin

Purpose

Topical hoof ointment to protect, prevent and heal most common hoof related issues

Use

Hoof Doctor Promotes and Maintains:

- Healthy moisture level of the hoof in any climate
- Aid to eliminate sensitivity of tender feet
- Aid in making the hoof elastic and flexible
- Preserving healthy hoof structure and growth
- Makes hoof and sole more durable
- Effective aid in healing:

white line disease;
abscesses;
thrush / canker;
quarter cracks / split hooves;
corns;
and other most common issues associated with the hoof sole and frog

SUITABLE FOR ALL HOOF TYPES

Warnings

FOR HOOF USE ONLY.
KEEP OUT OF REACH CHILDREN AND PETS. NOT FOR HUMAN OR CONSUMPTIONS.
Avoid contact with eyes and excessive breathing. In case of contact, immediately flush eye with plenty of water. Do not freeze (34°F / 1°C minimum).

Application

- After cleaning the hoof, apply Hoof Doctor to the coronet, hoof wall, sole and frog
- For sever conditions, apply twice daily for at least a week
- For preventive measures, apply thrice weekly